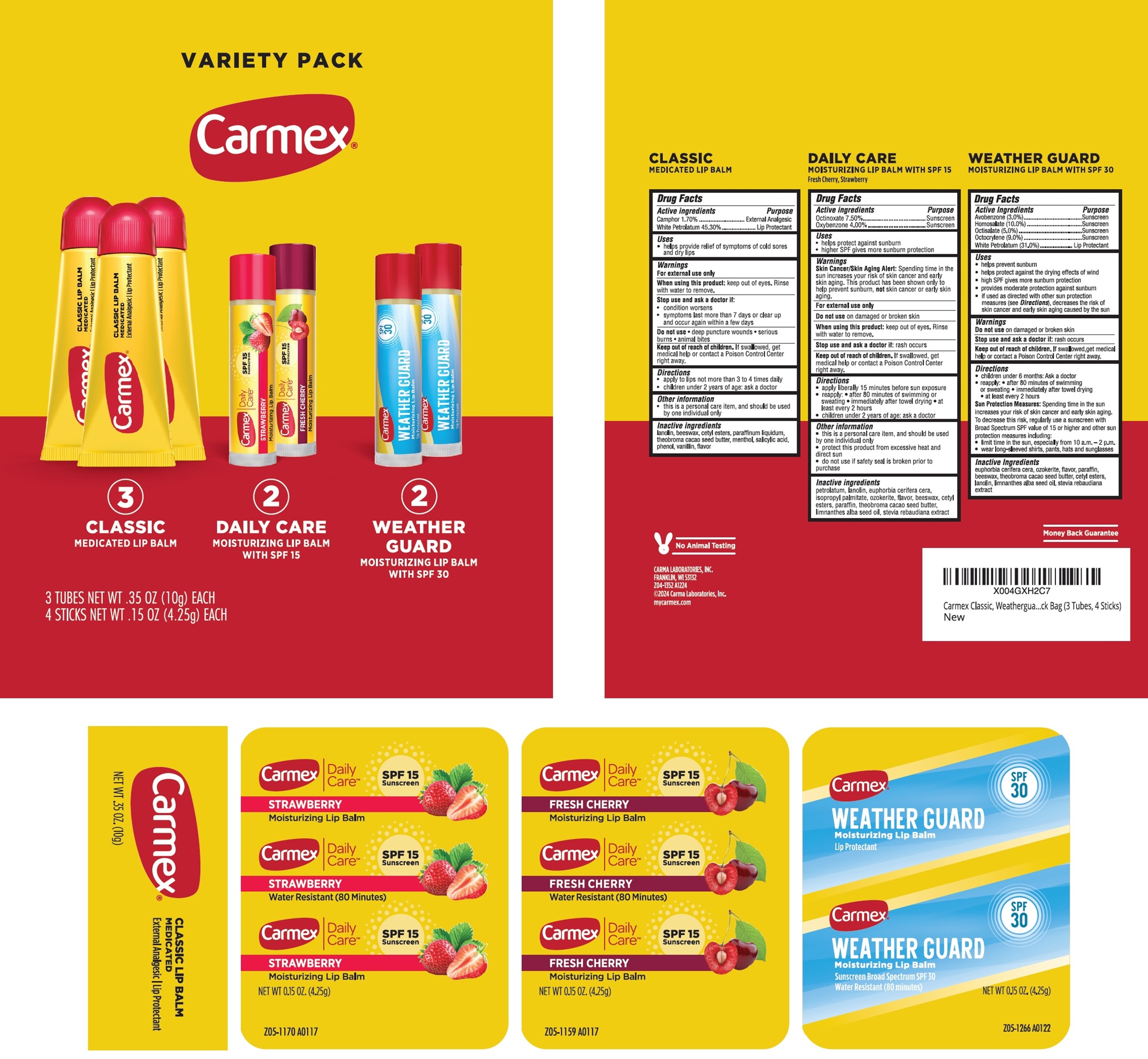 DRUG LABEL: Carmex Variety Pack Classic Medicated Lip Balm Daily Care Lip Balm SPF
NDC: 10210-0092 | Form: KIT | Route: TOPICAL
Manufacturer: Carma Laboratories, Inc.
Category: otc | Type: HUMAN OTC DRUG LABEL
Date: 20250320

ACTIVE INGREDIENTS: CAMPHOR (SYNTHETIC) 1.7 g/100 g; WHITE PETROLATUM 45.3 g/100 g; OCTINOXATE 75 mg/1 g; OXYBENZONE 40 mg/1 g; OCTINOXATE 75 mg/1 g; OXYBENZONE 40 mg/1 g; AVOBENZONE 30 mg/1 g; HOMOSALATE 100 mg/1 g; OCTISALATE 50 mg/1 g; OCTOCRYLENE 90 mg/1 g; WHITE PETROLATUM 310 mg/1 g
INACTIVE INGREDIENTS: LANOLIN; YELLOW WAX; CETYL ESTERS WAX; MINERAL OIL; MENTHOL, UNSPECIFIED FORM; SALICYLIC ACID; PHENOL; VANILLIN; PETROLATUM; LANOLIN; ISOPROPYL PALMITATE; YELLOW WAX; CETYL ESTERS WAX; PARAFFIN; MEADOWFOAM SEED OIL; PETROLATUM; LANOLIN; ISOPROPYL PALMITATE; YELLOW WAX; CETYL ESTERS WAX; PARAFFIN; MEADOWFOAM SEED OIL; PARAFFIN; YELLOW WAX; CETYL ESTERS WAX; LANOLIN; MEADOWFOAM SEED OIL

Carmex Variety Pack - Classic Medicated Lip Balm, Daily Care Lip Balm SPF

Active ingredients

Camphor 1.70%

White Petrolatum 45.30%

Purpose

External Analgesic

Lip Protectant

Uses

- helps provide relief of symptoms of cold sores and dry lips

Warnings

For external use only

When using this product:

keep out of eyes. Rinse with water to remove.

Stop use and ask a doctor if:

- condition worsens
- symptoms last more than 7 days or clear up and occur again within a few days

Do not use

- deep puncture wounds
- serious burns
- animal bites

Keep out of reach of children.

If swallowed, get medical help or contact a Poison Control Center right away.

Directions

• apply to lips not more than 3 to 4 times daily

• children under 2 years of age: ask a doctor

Other information

• this is a personal care item, and should be used by one individual only

Inactive ingredients

lanolin, beeswax, cetyl esters, paraffinum liquidum, theobroma cacao seed butter, menthol, salicylic acid, phenol, vanillin, flavor

Active ingredients

Octinoxate 7.50%

Oxybenzone 4.00%

Purpose

Sunscreen

Uses

- helps protect against sunburn
- higher SPF gives more sunburn protection

Warnings

Skin Cancer/Skin Aging Alert:Spending time in the sun increases your risk of skin cancer and early skin aging. This product has been shown only to help prevent sunburn, not skin cancer or early skin aging.

For external use only

Do not use

on damaged or broken skin

When using this product:

keep out of eyes. Rinse with water to remove.

Stop use and ask a doctor if:

rash occurs

Keep out of reach of children.

If swallowed, get medical help or contact a Poison Control Center right away.

Directions

• apply liberally 15 minutes before sun exposure

• reapply: • after 80 minutes of swimming or sweating

• immediately after towel drying • at least every 2 hours

• children under 2 years of age: ask a doctor

Other information

• this is a personal care item, and should be used by one individual only

• protect this product from excessive heat and direct sun

• do not use if safety seal is broken prior to purchase

Inactive ingredients

petrolatum, lanolin, euphorbia cerifera cera, isopropyl palmitate, ozokerite, flavor, beeswax, cetyl esters, paraffin, theobroma cacao seed butter, limnanthes alba seed oil, stevia rebaudiana extract

Active Ingredients

Avobenzone (3.0%)

Homosalate (10.0%)

Octisalate (5.0%)

Octocrylene (9.0%)

White Petrolatum (31.0%)

Purpose

Sunscreen

Lip Protectant

Uses

- helps prevent sunburn
- hepls protect against the drying effects of wind
- high SPF gives more sunburn protection
- provides moderate protection against sunburn
- if used as directed with other sun protection measures (see Directions), decreases the risk of skin cancer and early skin aging caused by the sun

Warnings

Do not use

on damaged or broken skin

Stop use and ask a doctor if:

rash occurs

Keep out of reach of children.

If swallowed, get medical help or contact a Poison Control Center right away.

Directions

- children under 6 months: Ask a doctor
- reapply:
- after 80 minutes of swimming or sweating
- immediately after towel drying
- at least every 2 hours

Sun Protection Measures:Spending time in the sun increases your risk of skin cancer and early skin aging. To decrease this risk, regularly use a sunscreen with Broad Spectrum SPF value of 15 or higher and other sun protection measures including:

- limit time in the sun, especially from 10 a.m. - 2 p.m.
- wear long-sleeved shirts, pants, hats and sunglasses

Inactive ingredients

euphorbia cerifera cera, ozoketite, flavor, paraffin, beeswax, Theobroma cacao seed butter, cetyl esters, lanolin, limnanthes alba seed oil, stevia rebaudiana extract